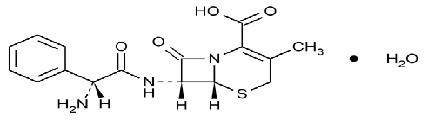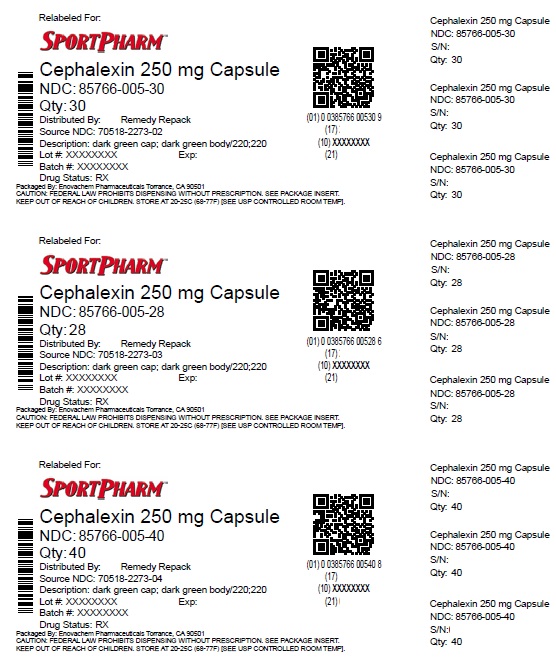 DRUG LABEL: Cephalexin
NDC: 85766-005 | Form: CAPSULE
Manufacturer: Sportpharm LLC
Category: prescription | Type: HUMAN PRESCRIPTION DRUG LABEL
Date: 20260203

ACTIVE INGREDIENTS: CEPHALEXIN 250 mg/1 1
INACTIVE INGREDIENTS: MAGNESIUM STEARATE; FD&C BLUE NO. 1; FD&C RED NO. 40; D&C YELLOW NO. 10; GELATIN; SODIUM LAURYL SULFATE; TITANIUM DIOXIDE; SILICON DIOXIDE; SHELLAC; PROPYLENE GLYCOL; AMMONIA; POTASSIUM HYDROXIDE; FERROSOFERRIC OXIDE; ANHYDROUS LACTOSE

HIGHLIGHTS OF PRESCRIBING INFORMATION

These highlights do not include all the information needed to use CEPHALEXIN CAPSULES safely and effectively. See full prescribing information for CEPHALEXIN CAPSULES.
CEPHALEXIN capsules, for oral use
Initial U.S. Approval: 1971

1 INDICATIONS & USAGE

Cephalexin is a cephalosporin antibacterial drug indicated for the treatment of the following infections caused by susceptible isolates of designated bacteria:

- Respiratory tract infection (1.1)
- Otitis media (1.2)
- Skin and skin structure infections (1.3)
- Bone infections (1.4)
- Genitourinary tract infections (1.5)

To reduce the development of drug-resistant bacteria and maintain the effectiveness of cephalexin and other antibacterial drugs, Cephalexin should be used only to treat infections that are proven or strongly suspected to be caused by bacteria. (1.6)

2 DOSAGE & ADMINISTRATION

Adults and patients at least 15 years of age | The usual dose is 250 mg every 6 hours, but a dose of 500 mg every 12 hours may be administered (2.1)
Pediatric patients (over 1 year of age) | - Otitis media: 75 to 100 mg/kg in equally divided doses every 6 hours (2.2) - All other indications: 25 to 50 mg/kg given in equally divided doses (2.2) - In severe infections: 50 to 100 mg/kg may be administered in equally divided doses (2.2)

- Duration of therapy ranges from 7 to14 days depending on the infection type and severity. (2)
- Dosage adjustment is required in patients with severe and end stage renal disease (ESRD) defined as creatinine clearance below 30 mL/min. (2.3)

3 DOSAGE FORMS & STRENGTHS

Capsules: 250 mg (3)

4 CONTRAINDICATIONS

Patients with known hypersensitivity to cephalexin or other members of the cephalosporin class of antibacterial drugs. (4)

5 WARNINGS AND PRECAUTIONS

- Serious hypersensitivity (anaphylactic) reactions: Prior to use, inquire regarding history of hypersensitivity to beta-lactam antibacterial drugs. Discontinue the drug if signs or symptoms of an allergic reaction occur and institute supportive measures. (5.1)
- Clostridium difficile-associated diarrhea (CDAD): Evaluate if diarrhea occurs. (5.2)
- Direct Coomb’s Test Seroconversion: If anemia develops during or after cephalexin therapy, evaluate for drug-induced hemolytic anemia. (5.3)
- Seizure Potential: Use lower dose in patients with renal impairment. (5.4)

6 ADVERSE REACTIONS

The most common adverse reactions associated with cephalexin include diarrhea, nausea, vomiting, dyspepsia and abdominal pain. (6)

To report SUSPECTED ADVERSE REACTIONS, contact Ascend Laboratories, LLC at 1-877-ASC-RX01 (877-272-7901) or FDA at 1-800-FDA-1088 or www.fda.gov/medwatch.

7 DRUG INTERACTIONS

- Metformin: increased metformin concentrations. Monitor for hypoglycemia. (7.1)
- Probenecid- The renal excretion of cephalexin is inhibited by probenecid. Co-administration of probenecid with cephalexin is not recommended. (7.2)
- Administration of cephalexin may result in a false-positive reaction glucose in the urine. (7.3)

8 USE IN SPECIFIC POPULATIONS

Renal Impairment: Monitor patients longer for toxicity and drug interactions due to delayed clearance. (8.6)

FULL PRESCRIBING INFORMATION

1 INDICATIONS & USAGE

1.1 Respiratory Tract Infections

Cephalexin is indicated for the treatment of respiratory tract infections caused by susceptible isolates of Streptococcus pneumoniaeand Streptococcus pyogenes.

1.2 Otitis Media

Cephalexin is indicated for the treatment of otitis media caused by susceptible isolates of Streptococcus pneumoniae, Haemophilus influenzae, Staphylococcus aureus, Streptococcus pyogenes, and Moraxella catarrhalis.

1.3 Skin and Skin Structure Infections

Cephalexin is indicated for the treatment of skin and skin structure infections caused by susceptible isolates of the following Gram-positive bacteria: Staphylococcus aureusand Streptococcus pyogenes.

1.4 Bone Infections

Cephalexin is indicated for the treatment of bone infections caused by susceptible isolates of Staphylococcus aureusand Proteus mirabilis.

1.5 Genitourinary Tract Infections

Cephalexin is indicated for the treatment of genitourinary tract infections, including acute prostatitis, caused by susceptible isolates of Escherichia coli, Proteus mirabilis, and Klebsiella pneumoniae.

1.6 Usage

To reduce the development of drug-resistant bacteria and maintain the effectiveness of cephalexin and other antibacterial drugs, Cephalexin should be used only to treat infections that are proven or strongly suspected to be caused by susceptible bacteria. When culture and susceptibility information is available, this information should be considered in selecting or modifying antibacterial therapy. In the absence of such data, local epidemiology and susceptibility patterns may contribute to the empiric selection of therapy.

2 DOSAGE & ADMINISTRATION

2.1 Adults and Pediatric Patients at Least 15 Years of Age

The usual dose of oral Cephalexin capsule, USP is 250 mg every 6 hours, but a dose of 500 mg every 12 hours may be administered. Treatment is administered for 7 to 14 days.

For more severe infections larger doses of oral Cephalexin capsules, USP may be needed, up to 4 grams daily in two to four equally divided doses.

2.2 Pediatric Patients (over 1 year of age)

The recommended total daily dose of oral Cephalexin capsules, USP for pediatric patients is 25 to 50 mg/kg given in equally divided doses for 7 to 14 days. In the treatment of β-hemolytic streptococcal infections, duration of at least 10 days is recommended. In severe infections, a total daily dose of 50 to 100 mg/kg may be administered in equally divided doses.

For the treatment of otitis media, the recommended daily dose is 75 to 100 mg/kg given in equally divided doses.

2.3 Dosage Adjustments in Adult and Pediatric Patients at Least 15 Years of Age with Renal Impairment

Administer the following dosing regimens for Cephalexin capsules, USP to patients with renal impairment [see Warnings and Precautions (5.4) and Use in Specific Populations (8.6)].

Table 1. Recommended Dose Regimen for Patients with Renal Impairment

Renal function | Dose regimen recommendation
Creatinine clearance >60mL/min. | No dose adjustment
Creatinine clearance 30 to 59 mL/min | No dose adjustment; maximum daily dose should not exceed 1 g
Creatinine clearance 15 to 29 mL/min | 250 mg, every 8 hours or every 12 hours
Creatinine clearance 5 to 14 mL/min not yet on dialysis* | 250 mg, every 24 hours
Creatinine clearance 1 to 4 mL/min not yet on dialysis* | 250 mg, every 48 hours or every 60 hours

*There is insufficient information to make dose adjustment recommendations in patients on hemodialysis.

3 DOSAGE FORMS & STRENGTHS

250 mg capsules: a white to off white powder filled into size 2 capsules (dark green cap and dark green body) that are imprinted with “220” on the both cap and body in edible black ink.

4 CONTRAINDICATIONS

Cephalexin is contraindicated in patients with known hypersensitivity to cephalexin or other members of the cephalosporin class of antibacterial drugs.

5 WARNINGS AND PRECAUTIONS

5.1 Hypersensitivity Reactions

Allergic reactions in the form of rash, urticaria, angioedema, anaphylaxis, erythema multiforme, Stevens- Johnson syndrome, or toxic epidermal necrolysis have been reported with the use of cephalexin. Before therapy with cephalexin is instituted, inquire whether the patient has a history of hypersensitivity reactions to cephalexin, cephalosporins, penicillins, or other drugs. Cross-hypersensitivity among beta-lactam antibacterial drugs may occur in up to 10% of patients with a history of penicillin allergy.
If an allergic reaction to cephalexin occurs, discontinue the drug and institute appropriate treatment.

5.2 Clostridium difficile-Associated Diarrhea

Clostridium difficile-associated diarrhea (CDAD) has been reported with use of nearly all antibacterial agents, including cephalexin, and may range in severity from mild diarrhea to fatal colitis. Treatment with antibacterial agents alters the normal flora of the colon leading to overgrowth of C. difficile.

C. difficile produces toxins A and B, which contribute to the development of CDAD. Hypertoxin-producing strains of C. difficile cause increased morbidity and mortality, as these infections can be refractory to antimicrobial therapy and may require colectomy. CDAD must be considered in all patients who present with diarrhea following antibiotic use. Careful medical history is necessary since CDAD has been reported to occur over two months after the administration of antibacterial agents.

If CDAD is suspected or confirmed, ongoing antibiotic use not directed against C. difficile may need to be discontinued. Appropriate fluid and electrolyte management, protein supplementation, antibiotic treatment of C. difficile, and surgical evaluation should be instituted as clinically indicated.

5.3 Direct Coombs’ Test Seroconversion

Positive direct Coombs’ tests have been reported during treatment with the cephalosporin antibacterial drugs including cephalexin. Acute intravascular hemolysis induced by cephalexin therapy has been reported. If anemia develops during or after cephalexin therapy, perform a diagnostic work-up for drug-induced hemolytic anemia, discontinue cephalexin and institute appropriate therapy.

5.4 Seizure Potential

Several cephalosporins have been implicated in triggering seizures, particularly in patients with renal impairment when the dosage was not reduced. If seizures occur, discontinue cephalexin. Anticonvulsant therapy can be given if clinically indicated.

5.5 Prolonged Prothrombin Time

Cephalosporins may be associated with prolonged prothrombin time. Those at risk include patients with renal or hepatic impairment, or poor nutritional state, as well as patients receiving a protracted course of antibacterial therapy, and patients receiving anticoagulant therapy. Monitor prothrombin time in patients at risk and manage as indicated.

5.6 Development of Drug-Resistant Bacteria

Prescribing cephalexin in the absence of a proven or strongly suspected bacterial infection is unlikely to provide benefit to the patient and increases the risk of the development of drug-resistant bacteria.

Prolonged use of cephalexin may result in the overgrowth of nonsusceptible organisms. Careful observation of the patient is essential. If superinfection occurs during therapy, appropriate measures should be taken.

6 ADVERSE REACTIONS

The following serious events are described in greater detail in the Warning and Precautions section:

- Hypersensitivity reactions [ see Warning and Precautions (5.1) ]
- Clostridium difficile-associated diarrhea [ see Warnings and Precautions (5.2) ]
- Direct Coombs’ Test Seroconversion [ see Warnings and Precautions (5.3) ]
- Seizure Potential [ see Warnings and Precautions (5.4) ]
- Effect on Prothrombin Activity [ see Warnings and Precautions (5.5) ]
- Development of Drug-Resistant Bacteria [ see Warnings and Precautions (5.6) ]

6.1 Clinical Trials Experience

Because clinical trials are conducted under widely varying conditions, adverse reaction rates observed in the clinical trials of a drug cannot be directly compared to rates in the clinical trials of another drug and may not reflect the rates observed in practice

In clinical trials, the most frequent adverse reaction was diarrhea. Nausea and vomiting, dyspepsia, gastritis, and abdominal pain have also occurred. As with penicillins and other cephalosporins, transient hepatitis and cholestatic jaundice have been reported.

Other reactions have included hypersensitivity reactions, genital and anal pruritus, genital candidiasis, vaginitis and vaginal discharge, dizziness, fatigue, headache, agitation, confusion, hallucinations, arthralgia, arthritis, and joint disorder. Reversible interstitial nephritis has been reported. Eosinophilia, neutropenia, thrombocytopenia, hemolytic anemia, and slight elevations in aspartate transaminase (AST) and alanine transaminase (ALT) have been reported.

In addition to the adverse reactions listed above that have been observed in patients treated with cephalexin, the following adverse reactions and other altered laboratory tests have been reported for cephalosporin class antibacterial drugs:

Other Adverse Reactions: Fever, colitis, aplastic anemia, hemorrhage, renal dysfunction, and toxic nephropathy.

Altered Laboratory Tests: Prolonged prothrombin time, increased blood urea nitrogen (BUN), increased creatinine, elevated alkaline phosphatase, elevated bilirubin, elevated lactate dehydrogenase (LDH), pancytopenia, leukopenia, and agranulocytosis.

7 DRUG INTERACTIONS

7.1 Metformin

Administration of cephalexin with metformin results in increased plasma metformin concentrations and decreased renal clearance of metformin.

Careful patient monitoring and dose adjustment of metformin is recommended in patients concomitantly taking cephalexin and metformin [ see Clinical Pharmacology (12.3)]

7.2 Probenecid

The renal excretion of cephalexin is inhibited by probenecid. Co-administration of probenecid with cephalexin is not recommended.

7.3 Interaction with Laboratory or Diagnostic Testing

A false-positive reaction may occur when testing for the presence of glucose in the urine using Benedict’s solution or Fehling’s solution.

8 USE IN SPECIFIC POPULATIONS

8.1 Pregnancy

Risk Summary
Available data from published epidemiologic studies and pharmacovigilance case reports over several decades with cephalosporin use, including cephalexin use in pregnant women have not established drug-associated risks of major birth defects, miscarriage, or adverse maternal or fetal outcomes (see Data).
Animal reproduction studies with mice and rats using oral doses of cephalexin that are 0.6- and 1.2-times the maximum recommended human dose (MRHD) based on body surface area during organogenesis revealed no evidence of harm to the fetus (see Data).
The estimated background risk of major birth defects and miscarriage for the indicated population is unknown. All pregnancies have a background risk of birth defect, loss, or other adverse outcomes. In the U.S. general population, the estimated background risk of major birth defects and miscarriage in clinically recognized pregnancies is 2% to 4% and 15% to 20%, respectively.

Data

Human Data

While available studies cannot definitively establish the absence of risk, published data from epidemiologic studies and postmarketing case reports over several decades have not identified a consistent association with cephalosporin use, including cephalexin, during pregnancy, and major birth defects, miscarriage, or other adverse maternal or fetal outcomes. Available studies have methodologic limitations, including small sample size, retrospective data collection, and inconsistent comparator groups.

Animal Data

In animal reproduction studies, pregnant mice and rats administered oral cephalexin doses of 250 or 500 mg/kg/day (approximately 0.6 and 1.2 times the MRHD) based on body surface area, respectively during the period of organogenesis showed no adverse effects on embryofetal development.

In a pre-and post-natal developmental toxicity study, pregnant rats that received oral doses of 250 or 500 mg/kg/day of cephalexin from Day 15 of pregnancy to litter Day 21 showed no adverse effects on parturition, litter size, or growth of offspring.

8.2 Lactation

Risk Summary

Data from a published clinical lactation study reports that cephalexin is present in human milk. The Relative Infant Dose (RID) is considered to be <1% of the maternal weight adjusted dose. There are no data on the effects of cephalexin on the breastfed child or on milk production.

The development of health benefits of breastfeeding should be considered along with the mother’s clinical need for cephalexin and any potential adverse effects on the breastfed child from cephalexin or from the underlying maternal condition.

8.4 Pediatric Use

The safety and effectiveness of cephalexin in pediatric patients was established in clinical trials for the dosages described in the dosage and administration section [see Dosage and Administration (2.2)]

8.5 Geriatric Use

Of the 701 subjects in 3 published clinical studies of cephalexin, 433 (62%) were 65 and over. No overall differences in safety or effectiveness were observed between these subjects and younger subjects, and other reported clinical experience has not identified differences in responses between the elderly and younger patients.

This drug is substantially excreted by the kidney, and the risk of toxic reactions to this drug may be greater in patients with impaired renal function. Because elderly patients are more likely to have decreased renal function, care should be taken in dose selection [ see Warnings and Precautions (5.4)]

8.6 Renal Impairment

Cephalexin should be administered with careful monitoring in the presence of renal impairment (creatinine clearance < 30 mL/min, with or without dialysis). Under such conditions, careful clinical observation and laboratory studies renal function monitoring should be conducted because safe dosage may be lower than that usually recommended [see Dosage and Administration (2.3)].Monitor patients longer for toxicity and drug interactions due to delayed clearance.

10 OVERDOSAGE

Symptoms of oral overdose may include nausea, vomiting, epigastric distress, diarrhea, and hematuria. In the event of an overdose, institute general supportive measures.

Forced diuresis, peritoneal dialysis, hemodialysis, or charcoal hemoperfusion have not been established as beneficial for an overdose of cephalexin.

11 DESCRIPTION

Cephalexin capsules, USP is a semisynthetic cephalosporin antibacterial drug intended for oral administration. It is 7-(D-α-Amino-α-phenylacetamido)-3-methyl-3-cephem-4-carboxylic acid monohydrate. Cephalexin has the molecular formula C16H17N3O4S•H2O and the molecular weight is 365.41.
Cephalexin has the following structural formula:

Each capsule contains cephalexin monohydrate equivalent to 250 mg, 333 mg, 500 mg, or 750 mg of cephalexin. The 250 mg, 333 mg, 500 mg and 750 mg capsules contain anhydrous lactose, colloidal silicon dioxide, magnesium stearate, FD & C Blue No. 1, D & C Yellow No. 10, gelatin, sodium lauryl sulphate, titanium dioxide. In addition, the 250 mg capsule contains FD & C Red No. 40; 333 mg and 750 mg Capsules contains FD & C Yellow No. 6. The imprinting ink contains; shellac, propylene glycol, strong ammonia solution and potassium hydroxide. Also black Iron oxide is used in 250mg, 333mg and 500mg and titanium dioxide is used in 750mg.

12 CLINICAL PHARMACOLOGY

12.1 Mechanism of Action

Cephalexin is a cephalosporin antibacterial drug [see Microbiology (12.4)]

12.3 Pharmacokinetics

Absorption:

Cephalexin is acid stable and may be given without regard to meals. Following doses of 250 mg, 500 mg, and 1 g, average peak serum levels of approximately 9, 18, and 32 mcg/mL, respectively, were obtained at 1 hour. Serum levels were detectable 6 hours after administration (at a level of detection of 0.2 mcg/mL).

Distribution:

Cephalexin is approximately 10% to 15% bound to plasma proteins.

Excretion:

Cephalexin is excreted in the urine by glomerular filtration and tubular secretion. Studies showed that over 90% of the drug was excreted unchanged in the urine within 8 hours. During this period, peak urine concentrations following the 250 mg, 500 mg, and 1 g doses were approximately 1000, 2200, and 5000 mcg/mL respectively.

Drug Interactions:

In healthy subjects given single 500 mg doses of cephalexin and metformin, plasma metformin mean Cmaxand AUC increased by an average of 34% and 24%, respectively, and metformin mean renal clearance decreased by 14%. No information is available about the interaction of cephalexin and metformin following multiple doses of either drug.

12.4 Microbiology

Mechanism of Action

Cephalexin is a bactericidal agent that acts by the inhibition of bacterial cell-wall synthesis.

Resistance

Methicillin-resistant staphylococci and most isolates of enterococci are resistant to cephalexin. Cephalexin is not active against most isolates of Enterobacter spp., Morganella morganii,and Proteus vulgaris.Cephalexin has no activity against Pseudomonas spp., or Acinetobacter calcoaceticus. Penicillin-resistant Streptococcus pneumoniaeis usually cross-resistant to beta-lactam antibacterial drugs.

Antimicrobial Activity

Cephalexin has been shown to be active against most isolates of the following bacteria both in vitroand in clinical infections [ see Indications and Usage (1)]

Gram-positive bacteria

Staphylococcus aureus(methicillin-susceptible isolates only)

Streptococcus pneumoniae(penicillin-susceptible isolates)

Gram-negative bacteria

Escherichia coli

Haemophilus influenzae

Klebsiella pneumoniae

Moraxella catarrhalis

Proteus mirabilis

Susceptibility Testing
For specific information regarding susceptibility test interpretive criteria and associated test methods and quality control standards recognized by FDA for this drug, please see: https://www.fda.gov/STIC.

13 NONCLINICAL TOXICOLOGY

13.1 Carcinogenesis & Mutagenesis & Impairment Of Fertility

Lifetime studies in animals have not been performed to evaluate the carcinogenic potential of cephalexin. Tests to determine the mutagenic potential of cephalexin have not been performed. In male and female rats, fertility and reproductive performance were not affected by cephalexin oral doses up to 1.5 times the highest recommended human dose based upon body surface area.

16 HOW SUPPLIED/STORAGE AND HANDLING

Cephalexin capsules, USP, are supplied as follows:

The 250 mg capsules are a white to off white powder filled into size 2 capsules (dark green cap and dark green body) that are imprinted with “220” on the both cap and body in edible black ink. They are available as follows:

PACKAGING: 30 in 1 BOTTLE PLASTIC NDC 85766-005-30 (relabeled from NDC 70518-2273-02)

PACKAGING: 28 in 1 BOTTLE PLASTIC NDC 85766-005-28 (relabeled from NDC 70518-2273-03)

PACKAGING: 40 in 1 BOTTLE PLASTIC NDC 85766-005-40 (relabeled from NDC 70518-2273-04)

Store at 20°C to 25°C (68°F to77°F); excursions permitted to 15 to 30°C (59 to 86°F) [see USP Controlled Room Temperature].

17 PATIENT COUNSELING INFORMATION

Allergic Reactions
Advise patients that allergic reactions, including serious allergic reactions, could occur and that serious reactions require immediate treatment. Ask the patient about any previous hypersensitivity reactions to cephalexin, other beta-lactams (including cephalosporins) or other allergens (5.1)

Diarrhea
Advise patients that diarrhea is a common problem caused by antibacterial drugs and usually resolves when the drug is discontinued. Sometimes, frequent watery or bloody diarrhea may occur and may be a sign of a more serious intestinal infection. If severe watery or bloody diarrhea develops, advise patients to contact their healthcare provider

Antibacterial Resistance
Counsel patients that antibacterial drugs including cephalexin, should only be used to treat bacterial infections. They do not treat viral infections (e.g., the common cold). When cephalexin is prescribed to treat a bacterial infection, tell patients that although it is common to feel better early in the course of therapy, the medication should be taken exactly as directed. Skipping doses or not completing the full course of therapy may (1) decrease the effectiveness of the immediate treatment and (2) increase the likelihood that bacteria will develop resistance and will not be treatable by cephalexin or other antibacterial drugs in the future.

Distributed by:

Sportpharm LLC

379 Van Ness Ave 1401,

Torrance, CA 90501

Relabeled by:

Enovachem PHARMACEUTICALS

Torrance, CA 90501